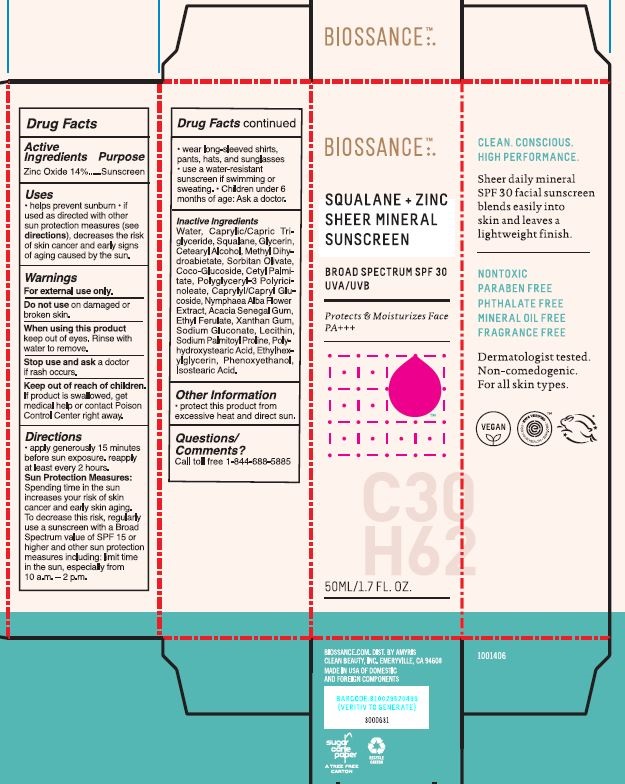 DRUG LABEL: SQUALANE ZINC SHEER MINERAL SUNSCREEN
NDC: 73517-125 | Form: CREAM
Manufacturer: Amyris, Inc
Category: otc | Type: HUMAN OTC DRUG LABEL
Date: 20220107

ACTIVE INGREDIENTS: ZINC OXIDE 140 mg/1 mL
INACTIVE INGREDIENTS: XANTHAN GUM; CETYL PALMITATE; NYMPHAEA ALBA FLOWER; PHENOXYETHANOL; SODIUM PALMITOYL PROLINE; ETHYLHEXYLGLYCERIN; COCO GLUCOSIDE; POLYGLYCERYL-3 RICINOLEATE; SQUALANE; POLYHYDROXYSTEARIC ACID (2300 MW); SODIUM GLUCONATE; CAPRYLYL/CAPRYL OLIGOGLUCOSIDE; GLYCERIN; ETHYL FERULATE; ISOSTEARIC ACID; ACACIA; WATER; CETOSTEARYL ALCOHOL; MEDIUM-CHAIN TRIGLYCERIDES; SORBITAN OLIVATE; METHYL DIHYDROABIETATE; LECITHIN, SUNFLOWER

SQUALANE + ZINC SHEER MINERAL SUNSCREEN

Purpose

Zinc Oxide 14% Sunscreen

Uses Warnings Directions

Helps prevent sunburn

if used as directed with other sun protection measures (see directions), decreases the risk of skin cancer and early signs of aging caused by the sun

Warnings

For external use only

Do not use on damaged or broken skin

When using this product keep out of eyes Rinse with water to remove

Stop use and ask a doctor if rash occurs

Keep out of reach of children if product is swallwed get medical help or contact Poison Control Center right away

Directions

apply generously 15 minutes before sun exposure. reapply at least every 2 hours

Sun Protection Measures

Spendign time in the sun increases your risk of skin cancer and early skin aging. To decrease this risk, regularly use a sunscreen with a BRoad Spectrum value of SPF 15 or higher and other sun protections measures including: limit time in the sun, especially from 10 am - 2pm

wear long-sleeved shirts, pants, hats, and sunglasses

use a water resistant sunscreen if swimming or sweating

children under 6 months of age ask a doctor.

Inactive Ingredients:

Inactive Ingredients: Water, Caprylic/Capric Triglyceride, Squalane, Glycerin, Cetearyl Alcohol, Methyl Dihydroabietate, Sorbitan Olivate, Coco-Glucoside, Cetyl Palmitate, Polyglyceryl-3 Polyricinoleate, Caprylyl/Capryl Glucoside, Nymphaea Alba Flower Extract, Acacia Senegal Gum, Ethyl Ferulate, Xanthan Gum, Sodium Gluconate, Lecithin, Sodium Palmitoyl Proline, Polyhydroxystearic Acid, Ethylhexylglycerin, Phenoxyethanol, Isostearic Acid.

Other Information

protect this product from excessive heat and direct sun